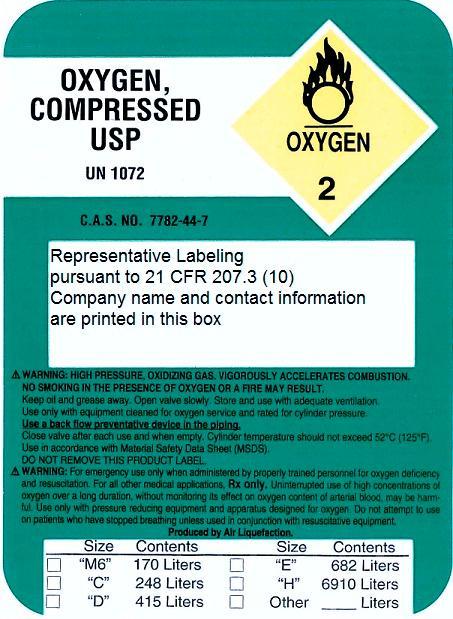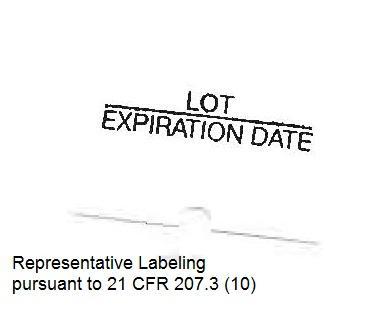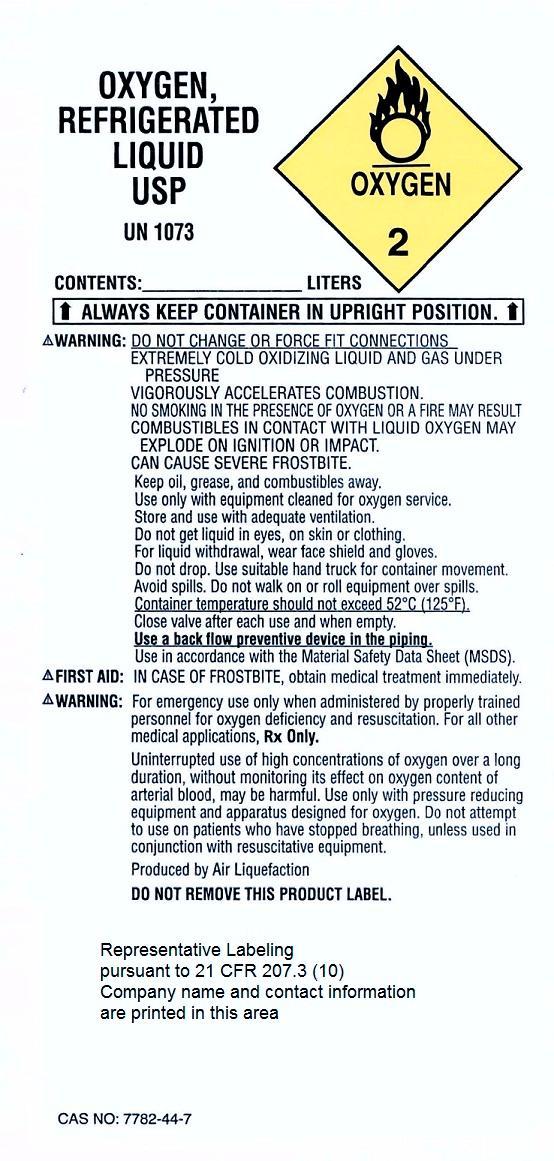 DRUG LABEL: Oxygen
NDC: 43482-1728 | Form: GAS
Manufacturer: Reliable Medical Inc.
Category: prescription | Type: HUMAN PRESCRIPTION DRUG LABEL
Date: 20140617

ACTIVE INGREDIENTS: Oxygen 99 L/100 L

Oxygen